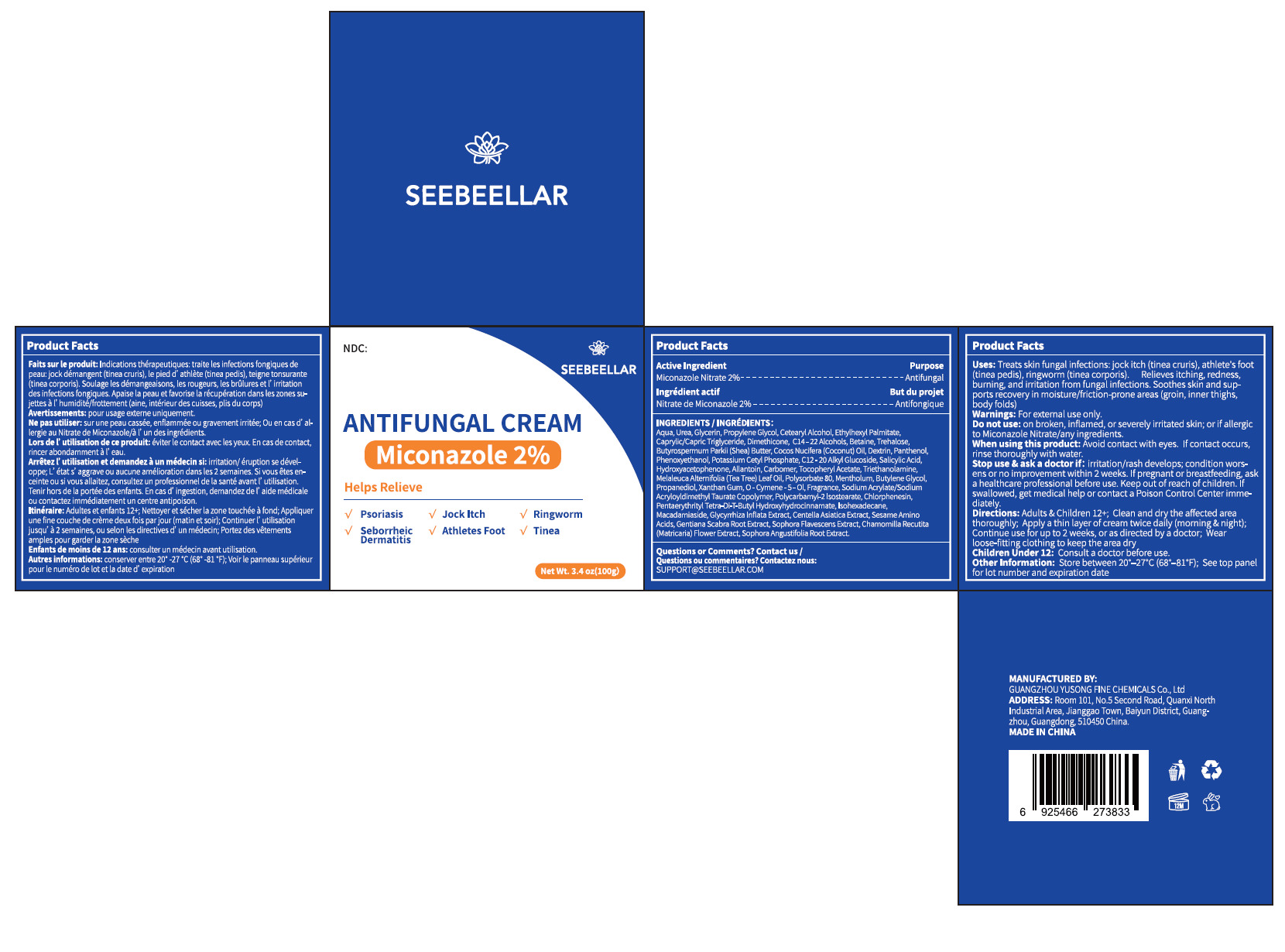 DRUG LABEL: seebeellar antifungal cream 2% miconazole
NDC: 84558-013 | Form: OINTMENT
Manufacturer: GUANGZHOU YUSONG FINE CHEMICLS Co., Ltd
Category: otc | Type: HUMAN OTC DRUG LABEL
Date: 20251009

ACTIVE INGREDIENTS: MICONAZOLE NITRATE 2 g/100 g
INACTIVE INGREDIENTS: AQUA; UREA; GLYCERIN; PROPYLENE GLYCOL; CETEARYL ALCOHOL; ETHYLHEXYL PALMITATE; CAPRYLIC/CAPRIC TRIGLYCERIDE; DIMETHICONE; C14-22 ALCOHOLS; BETAINE; TREHALOSE; BUTYROSPERMUM PARKII (SHEA) BUTTER; COCOS NUCIFERA (COCONUT) OIL; DEXTRIN, CORN; PANTHENOL; PHENOXYETHANOL; POTASSIUM CETYL PHOSPHATE; C12-20 ALKYL GLUCOSIDE; SALICYLIC ACID; HYDROXYACETOPHENONE; ALLANTOIN; CARBOMER; CENTELLA ASIATICA TRITERPENOIDS; PROPANEDIOL; MELALEUCA ALTERNIFOLIA (TEA TREE) LEAF OIL; MENTHOL; BUTYLENE GLYCOL; TRIETHANOLAMINE; O-CYMEN-5-OL; POLYSORBATE 80; CLOVE; CHLORPHENESIN; PENTAERYTHRITYL TETRA-DI-T-BUTYL HYDROXYHYDROCINNAMATE; XANTHAN GUM; SOPHORA FLAVESCENS ROOT; CHAMOMILE; POLYGLYCERYL-2 ISOSTEARATE; MADECASSOSIDE; ISOHEXADECANE; ALPHA-TOCOPHEROL ACETATE; GENTIANA SCABRA ROOT

84558-013

Active Ingredient(s)

MICONAZOLE NITRATE 2%

Purpose

Antifungal

Use

Uses: Treats skin fungal infections: jock itch (tinea cruris), athlete's foot
(tinea pedis), ringworm (tinea corporis).Relieves itching, redness,
burning, and irritation from fungal infections. Soothes skin and sup-
ports recovery in moisture/friction-prone areas (groin, inner thighs,
body folds)

Warnings

Warnings: For external use only.

Do not use: on broken, iflamed, or severely rritated skin; or if allergic
to Miconazole Nitrate/any ingredients.

When using this product: Avoid contact with eyes. If contact occurs,
rinse thoroughly with water.

Stop use & ask a doctor if: iritation/rash develops; condition wors-
ens or no improvement within 2 weeks. If pregnant or breastfeeding, ask
a healthcare professional before use. Keep out of reach of children. If
swallowed, get medical help or contact a Poison Control Center imme-
diately.

Children Under 12: Consult a doctor before use.

Directions

Directions: Adults & Children 12+; Clean and dry the affected area
thoroughly; Apply a thin layer of cream twice daily (morning & night);
Continue use for up to 2 weeks, or as directed by a doctor; Wear
loose-fitting clothing to keep the area dry

Other information

Other Information: Store between 20° -27°C (68° -81°F); See top panel
for lot number and expiration date

Inactive ingredients

Aqua, Urea, Glycerin, Propylene Glycol, Cetearyl Alcohol, Ethylhexyl Palmitate,
Caprylic/Capric Triglyceride, Dimethicone, C14- 22 Alcohols, Betaine, Trehalose,
Butyrospermum Parki (Shea) Butter, Cocos Nucifera (Coconut) Oil, Dextrin, Panthenol,
Phenoxyethanol, Potassium Cetyl Phosphate, C12 - 20 Alkyl Glucoside, Salicylic Acid,
Hydroxyacetophenone, Allantoin, Carbomer, Tocopheryl Acetate, Triethanolamine,
Melaleuca Alternifolia (Tea Tree) Leaf oil, Polysorbate 80 Mentholum, Butylene Glycol,
Propanediol, Xanthan Gum, 0- Cymene-5- Ol, Fragrance, Sodium Acrylate/Sodium
Acryloyldimethyl Taurate Copolymer, Polycarbamy-2 Isostearate, Chlorphenesin,
Pentaerythrityl Tetra- Di-T-Butyl Hydroxyhydrocinnamate, lsohexadecane,
Macadamiaside, Glyrhiza Inflata Extract, Centella Asiatica Extract, Sesame Amino
Acids, Gentiana Scabra Root Extract, Sophora Flavescens Extract, Chamomilla Recutita
(Matricaria) Flower Extract, Sophora Angustifolia Root Extract.